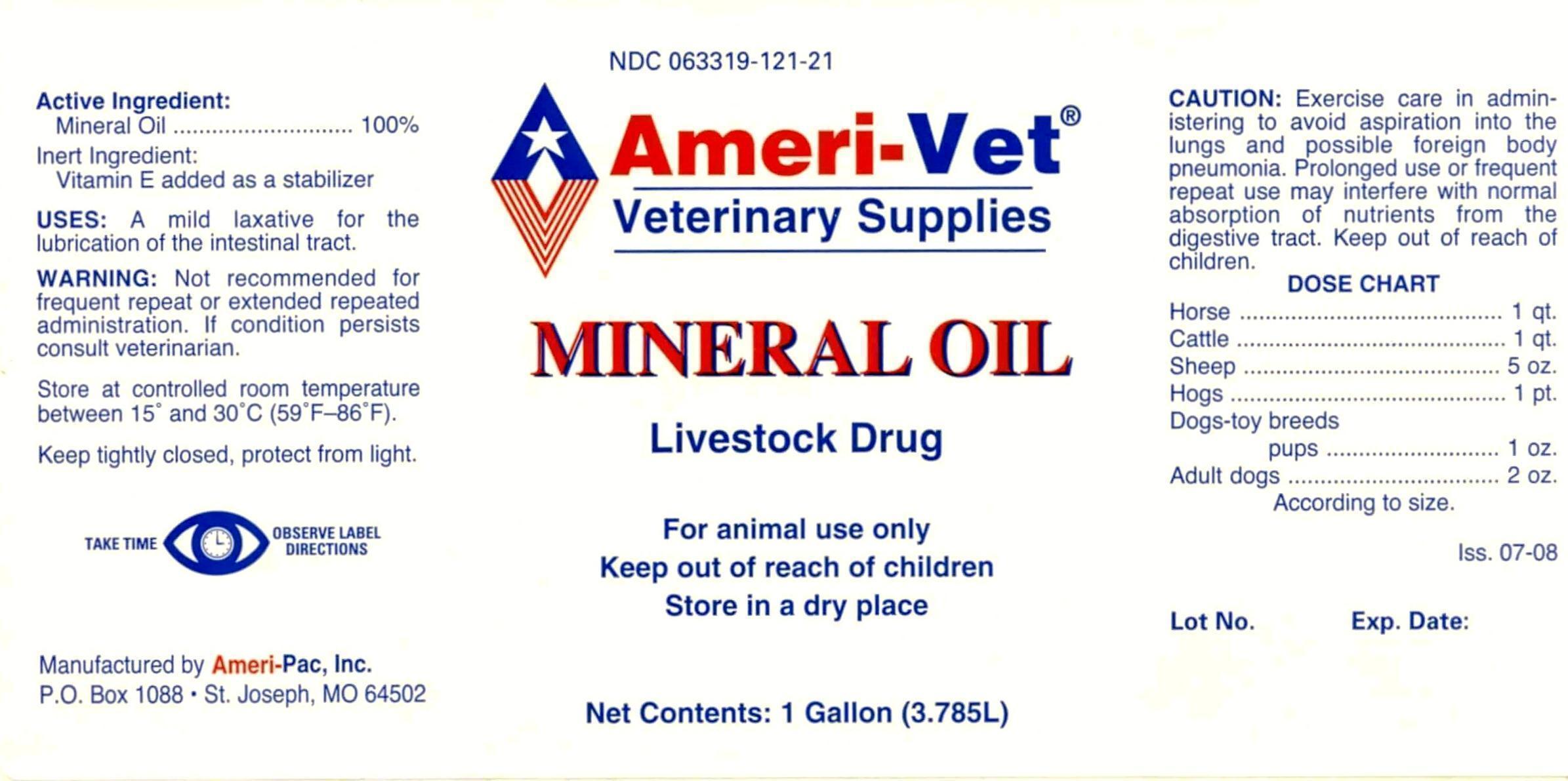 DRUG LABEL: MINERAL OIL, Light
NDC: 63319-121 | Form: LIQUID
Manufacturer: Ameri-Vet
Category: animal | Type: OTC ANIMAL DRUG LABEL
Date: 20131024

ACTIVE INGREDIENTS: LIGHT MINERAL OIL 3.45 kg/3.45 kg

Ameri-Vet MINERAL OIL

NDC 063319-121-21 Ameri-Vet Veterinary Supplies MINERAL OIL

Livestock Drug

For animal use only

Keep out of reach of children

Store in a dry place

NET CONTENTS: 1 Gallon (3.785L)

Active Ingredient:

Mineral Oil............................. 100%

Inert Ingredient:

Vitamin E added as a stabilizer

USES:

A mild laxative for the lubrication of the intestinal tract.

WARNING:

Not recommended for frequent repeat or extended repeated administration. If condition persists consult veterinarian.

STORAGE AND HANDLING

Store at controlled room temperature between 15º AND 30ºC (59ºF-86ºF).

Keep tightly closed, protect from light.

TAKE TIME OBSERVE LABEL DIRECTIONS

Manufacatured by Ameri-Pac, Inc.

P.O. Box 1088 St. Joseph, MO 64502

CAUTION:

Excerise care in administering to avoid aspiration into the lungs and possible foreign body pneumonia. Prolonged use or frequent repeat use may interfere with normal absorption of nutrients from the digestive tract. Keep out of reach of children.

DOSE CHART

Horse…………………………………………1 qt.

Cattle…………………………………………1 qt.

Sheep…………………………………….….5 oz.

Hogs…………………………………….…….1 pt.

Dogs-toy breeds

pups......................1 oz.

Adult dogs.………………………….…...2 oz.

According to size.

Iss. 07-08

Lot No. Exp Date: